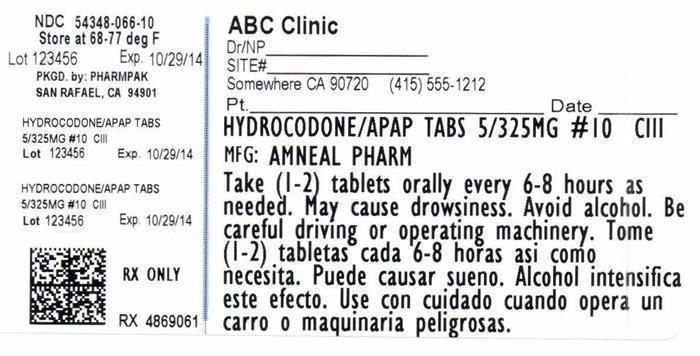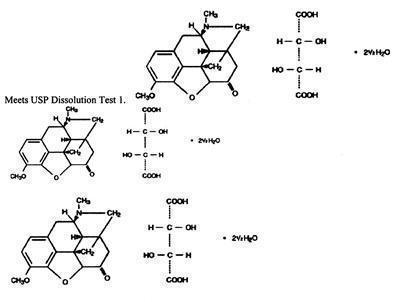 DRUG LABEL: HYDROCODONE/APAP
                
                
NDC: 54348-066 | Form: TABLET
Manufacturer: PharmPak, Inc.
Category: prescription | Type: HUMAN PRESCRIPTION DRUG LABEL
Date: 20150115
DEA Schedule: CII

ACTIVE INGREDIENTS: HYDROCODONE BITARTRATE 5 mg/1 1; ACETAMINOPHEN 325 mg/1 1
INACTIVE INGREDIENTS: SILICON DIOXIDE; CROSPOVIDONE; MAGNESIUM STEARATE; CELLULOSE, MICROCRYSTALLINE; POVIDONE; STARCH, CORN; STEARIC ACID

Description Hydrocodone Bitartrate and Acetaminophen Tablets, USP

CII Rx only

Hydrocodone Bitartrate and Acetaminophen Tablets, USP are supplied in tablet form for oral administration.

Hydrocodone bitartrate is an opioid analgesic and antitussive and occurs as fine, white crystals or as a crystalline powder. It is affected by light. The chemical name is 4,5α-Epoxy-3-methoxy-17-methylmorphinan-6-one tartrate (1:1) hydrate (2:5). It has the following structural formula: Acetaminophen, 4-hydroxyacetanilide, a slightly bitter, white, odorless, crystalline powder, is a non-opiate, non-salicylate analgesic and antipyretic. It has the following structural formula:

Each Hydrocodone Bitartrate and Acetaminophen Tablet, USP contains:

In addition, each tablet contains the following inactive ingredients: colloidal silicon dioxide, crospovidone, magnesium stearate, microcrystalline cellulose, povidone, pregelatinized starch and stearic acid.

Meets USP Dissolution Test 1.

Hydrocodone Bitartrate and Acetaminophen Tablets, USP, contain hydrocodone bitartrate 5 mg and acetaminophen 325 mg. They are supplied as white to off-white, scored, oblong biconvex tables, debossed "lP109" on obverse and bisected on the reverse.

Clinical Pharmacology

Hydrocodone is a semisynthetic opioid analgesic and antitussive with multiple actions qualitatively similar to those of codeine. Most of these involve the central nervous system and smooth muscle. The precise mechanism of action of hydrocodone and other opiates is not known, although it is believed to relate to the existence of opiate receptors in the central nervous system. In addition to analgesia, opioids may produce drowsiness, changes in mood and mental clouding.
The analgesic action of acetaminophen involves peripheral influences, but the specific mechanism is as yet undetermined. Antipyretic activity is mediated through hypothalamic heat regulating centers. Acetaminophen inhibits prostaglandin synthetase. Therapeutic doses of acetaminophen have negligible effects on the cardiovascular or respiratory systems; however, toxic doses may cause circulatory failure and rapid, shallow breathing.

Pharmacokinetics

The behavior of the individual components is described below.
Hydrocodone:
Following a 10 mg oral dose of hydrocodone administered to five adult male subjects, the mean peak concentration was 23.6 ± 5.2 ng/mL. Maximum serum levels were achieved at 1.3 ± 0.3 hours and the half-life was determined to be 3.8 ± 0.3 hours. Hydrocodone exhibits a complex pattern of metabolism including O-demethylation, N-demethylation and 6-ketoreduction to the corresponding 6-a- and 6-ß-hydroxymetabolites.
See OVERDOSAGE for toxicity information.
Acetaminophen:
Acetaminophen is rapidly absorbed from the gastrointestinal tract and is distributed throughout most body tissues. The plasma half-life is 1.25 to 3 hours, but may be increased by liver damage and following overdosage. Elimination of acetaminophen is principally by liver metabolism (conjugation) and subsequent renal excretion of metabolites. Approximately 85% of an oral dose appears in the urine within 24 hours of administration, most as the glucuronide conjugate, with small amounts of other conjugates and unchanged drug.
See OVERDOSAGE for toxicity information.

Indications and Usage

Hydrocodone bitartrate and acetaminophen tablets, USP are indicated for the relief of moderate to moderately severe pain.

Contraindications

Hydrocodone bitartrate and acetaminophen tablets should not be administered to patients who have previously exhibited hypersensitivity to hydrocodone or acetaminophen, or any other component of this product.
Patients known to be hypersensitive to other opioids may exhibit cross-sensitivity to hydrocodone.

Warnings

Respiratory Depression:
At high doses or in sensitive patients, hydrocodone may produce dose-related respiratory depression by acting directly on the brain stem respiratory center. Hydrocodone also affects the center that controls respiratory rhythm, and may produce irregular and periodic breathing.
Head Injury and Increased Intracranial Pressure:
The respiratory depressant effects of opioids and their capacity to elevate cerebrospinal fluid pressure may be markedly exaggerated in the presence of head injury, other intracranial lesions or a pre-existing increase in intracranial pressure. Furthermore, opioids produce adverse reactions which may obscure the clinical course of patients with head injuries.
Acute Abdominal Conditions:
The administration of opioids may obscure the diagnosis or clinical course of patients with acute abdominal conditions.

Keep this and all medications out of reach of children.

Special Risk Patients:

As with any opioid analgesic agent, hydrocodone bitartrate and acetaminophen tablets should be used with caution in elderly or debilitated patients and those with severe impairment of hepatic or renal function, hypothyroidism, Addison's disease, prostatic hypertrophy or urethral stricture. The usual precautions should be observed and the possibility of respiratory depression should be kept in mind.
Cough Reflex:
Hydrocodone suppresses the cough reflex; as with all opioids, caution should be exercised when hydrocodone bitartrate and acetaminophen tablets are used postoperatively and in patients with pulmonary disease.
Hydrocodone, like all opioids, may impair the mental and/or physical abilities required for the performance of potentially hazardous tasks such as driving a car or operating machinery; patients should be cautioned accordingly.
Alcohol and other CNS depressants may produce an additive CNS depression, when taken with this combination product, and should be avoided.
Hydrocodone may be habit-forming. Patients should take the drug only for as long as it is prescribed, in the amounts
prescribed, and no more frequently than prescribed.
In patients with severe hepatic or renal disease, effects of therfRV should be monitored with serial liver and/or renal
function tests.
Patients receiving other opioids, antihistamines, antipsychotics, antianxiety agents, or other CNS depressants
(including alcohol) concomitantly with hydrocodone bitartrate and acetaminophen tablets may exhibit an additive CNS depression. When combined therapy is contemplated, the dose of one or both agents should be reduced.
The use of MAO inhibitors or tricyclic antidepressants with hldrocodone preparations may increase the effect of either the antidepressant or hydrocodone.
Acetaminophen may produce false-positive test results for urinary 5-hydroxyindoleacetic acid.
No adequate studies have been conducted in animals to determine whether hydrocodone or acetaminophen have a potential for carcinogenesis, mutagenesis, or impairment of fertility.
Pregnancy Category C:
There are no adequate and well-controlled studies in pregnant women, hydrocodone bitartrate and acetaminophen tablets should be used during pregnancy only if the potential benefit justifies the potential risk to the fetus.
Babies born to mothers who have been taking opioids regularly prior to delivery will be physically dependent. The
withdrawal signs include irritability and excessive crying, tremors, hyperactive reflexes, increased respiratory rate,
increased stools, sneezing, yawning, vomiting, and fever. The intensity of the syndrome does not always correlate
with the duration of maternal opioid use or dose. There is no consensus on the best method of managing withdrawal.
As with all opioids, administration of this product to the mother shortly before delivery may result in some degree of
respiratory depression in the newborn, especially if higher doses are used.
Acetaminophen is excreted in breast milk in small amounts, but the significance of its effects on nursing infants is not known. It is not known whether hydrocodone is excreted in human milk. Because many drugs are excreted in human milk and because of the potential for serious adverse reactions in nursing infants from hydrocodone and acetaminophen, a decision should be made whether to discontinue nursing or to discontinue the drug, taking into account the importance of the drug to the mother.
Safety and effectiveness in pediatric patients have not been established.
Clinical studies of hydrocodone bitartrate and acetaminophen did not include sufficient numbers of subjects aged 65
and over to determine whether they respond differently from younger subjects. Other reported clinical experience
has not identified differences in responses between the elderly and younger patients. In general, dose selection for an
elderly patient should be cautious, usually starting at the low end of the dosing range, reflecting the greater frequency of decreased hepatic, renal, or cardiac function, and of concomitanidisease or other drug therapy.
Hydrocodone and the major metabolites of acetaminophen are known to be substantially excreted by the kidney.
Thus the risk of toxic reactions may be greater in patients with impaired renal function due to the accumulation of
the parent compound and/or metabolites in the plasma. Because elderly patients are more likely to have decreased
renal function, care should be taken in dose selection, and it may be useful to monitor renal function.
Hydrocodone may cause confusion and over-sedation in the elderly; elderly patients generally should be started on
low doses ofhydrocodone bitartrate and acetaminophen tablets and observed closely.

Adverse Reactions

The most frequently reported adverse reactions are light-headedness, dizziness, sedation, nausea and vomiting. These effects seem to be more prominent in ambulatory than in non-ambulatory patients, and some of these adverse reactions may be alleviated if the patient lies down.
Other adverse reactions include:
Central Nervous System: Drowsiness, mental clouding, lethargy, impairment of mental and physical performance, anxiety, fear, dysphoria, psychic dependence, mood changes.
Gastrointestinal System: Prolonged administration of hydrocodone bitartrate and acetaminophen tablets may produce constipation.
Genitourinary System: Ureteral spasm, spasm of vesical sphincters and urinary retention have been reported with opiates.
Respiratory Depression: Hydrocodone bitartrate may produce dose-related respiratory depression by acting directly on the brain stem respiratory centers (see OVERDOSAGE).
Special Senses: Cases of hearing impairment or permanent loss have been reported predominantly in patients with chronic overdose.
Dermatological: Skin rash, pruritus.
The following adverse drug events may be borne in mind as potential effects of acetaminophen: allergic reactions, rash, thrombocytopenia, agranulocytosis. Potential effects of high dosage are listed in the OVERDOSAGE section.

Abuse and Dependency

Controlled Substance: Hydrocodone bitartrate and acetaminophen tablets are classified as a Schedule III controlled substance.
Abuse and Dependence: Psychic dependence, physical dependence, and tolerance may develop upon repeated administration of opioids; therefore, this product should be prescribed and administered with caution. However, psychic dependence is unlikely to develop when hydrocodone bitartarte and acetaminophen tablets are used for a short time for the treatment of pain.
Physical dependence, the condition in which continued administration of the drug is required to prevent the appearance of a withdrawal syndrome, assumes clinically significant proportions only after several weeks of continued opiod use, although some mild degree of physical dependence may develop after a few days of opioid therapy. Tolerance, in which increasingly large doses are required in order to produce the same degree of analgesia, is manifested initially by a shortened duration of analgesic effect, and subsequently by decreases in the intensity of analgesia. The rate of development of tolerance varies among patients.

Overdosage Signs and Symptoms

Following an acute overdosage, toxicity may result from hydrocodone or acetaminophen.

Hydrocodone: Serious overdose with hydrocodone is characterized by respiratory depression (a decrease in respiratory rate and/or tidal volume. Cheyne-Stokes respiration, cyanosis), extreme somnolence progressing to stupor or coma, skeletal muscle flaccidity, cold and clammy skin, and sometimes bradycardia and hypotension. In severe overdosage, apnea, circulatory collapse, cardiac arrest and death may occur.
Acetaminophen: In acetaminophen overdosage "Drug seeking" behavior is very common in addicts and drug abusers. Drug-seeking tactics include emergency calls or visits near the end of office hours, refusal to undergo appropriate examination, testing or referral, repeated "loss" of prescripti: dose-dependent, potentially fatal hepatic necrosis is the most serious adverse effect. Renal tubular necrosis, hypoglycemic coma, and thrombocytopenia may also occur.
Early symptoms following a potentially hepatotoxic overdosage may include: nausea, vomiting, diaphoresis and general malaise. Clinical and laboratory evidence of hepatic toxicity may not be apparent until 48 to 72 hours post-ingestion.
In adults, hepatic toxicity has rarely been reported with acute overdoses of less than 10 grams, or fatalities with less than 15 grams.

A single or multiple overdose with hydrocodone and acetaminophen is a potentially lethal polydrug overdose, and consultation with a regional poison control center is recommended.

Treatment for Overdosage

Immediate treatment includes support of cardiorespiratory function and measures to reduce drug absorption. Vomiting should be induced mechanically, or with syrup of ipecac, if the patient is alert (adequate pharyngeal and laryngeal reflexes). Oral activated charcoal (1 g/kg) should follow gastric emptying. The first dose should be accompanied by an appropriate cathartic. If repeated doses are used, the cathartic might be included with alternate doses as required. Hypotension is usually hypovolemic and should respond to fluids. Vasopressors and other supportive measures should be employed as indicated. A cuffed endotracheal tube should be inserted before gastric lavage of the unconscious patient and, when necessary, to provide assisted respiration.
Meticulous attention should be given to maintaining adequate pulmonary ventilation. In severe cases of intoxication, peritoneal dialysis, or preferably hemodialysis may be considered. If hypoprothrombinemia occurs due to acetaminophen overdose, vitamin K should be administered intravenously.
Naloxone, an opioid antagonist, can reverse respiratory depression and coma associated with opioid overdose. Naloxone hydrochloride 0.4 mg to 2 mg is given parenterally. Since the duration of action of hydrocodone may exceed that of the naloxone, the patient should be kept under continuous surveillance and repeated doses of the antagonist should be administered as needed to maintain adequate respiration. An opioid antagonist should not be administered in the absence of clinically significant respiratory or cardiovascular depression.
If the dose of acetaminophen may have exceeded 140 mg/kg, acetylcysteine should be administered as early as possible. Serum acetaminophen levels should be obtained, since levels four or more hours following ingestion help predict acetaminophen toxicity. Do not await acetaminophen assay results before initiating treatment. Hepatic enzymes should be obtained initially, and repeated at 24- hour intervals.
Methemoglobinemia over 30% should be treated with methylene blue by slow intravenous administration.
The toxic dose for adults for acetaminophen is 10 g.

Dosage and Administration

Dosage should be adjusted according to the severity of the pain and the response of the patient. However, it should be kept in mind that tolerance to hydrocodone can develop with continued use and that the incidence of untoward effects is dose related.
The usual adult dosage is one or two tablets every four to six hours as needed for pain.

Storage

Storage: Store at 25°C (77°F); excursions permitted to 15° to 30°C (59° to 86°) [see USP Controlled Room Temperature].
A Schedule CIII Opioid.

Protect from light.

HYDROCODONE/APAP TAB 5/325MG #10 C111 Label

NDC 54348-066-10
Store at 68-77 deg F
Lot 123456 Exp10/29/14
PKGD: by PHARMPAK
SAN RAFAEL, CA 94901
HYDROCODONE/APAP TABS
5/325MG # 10 C111
Lot 123456 Exp 10/29/14
Rx ONLY
Rx 4869061
ABC Clinic
Dr/NP __________
SITE# __________
Somewhere CA 90720 (415) 555-1212
Pt _________________ Date _______
HYDROCODONE/APAP TABS 5/325MG # 10 C111
MFG: AMNEAL PHARM
Take (1-2) tablets orally every 6-8 hours as needed. May cause drowsiness. Avoid alcohol. Be careful driving or operating machinery.